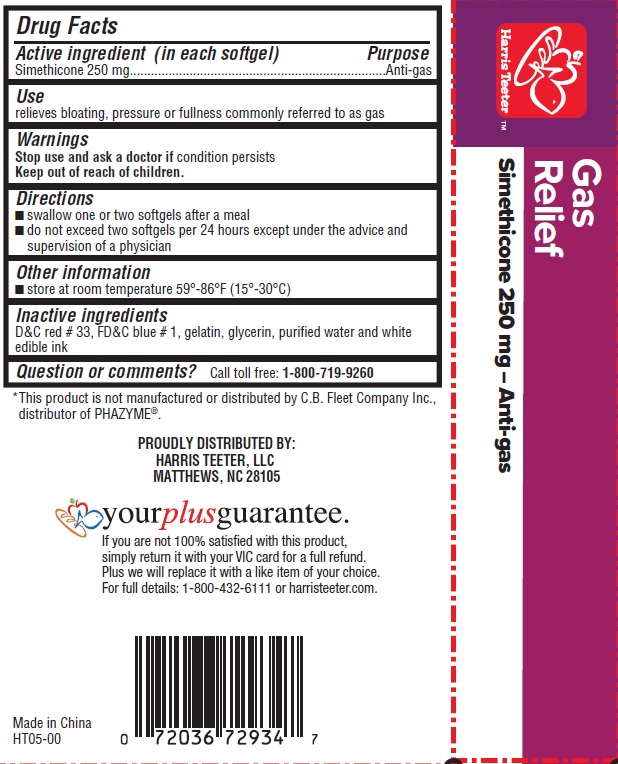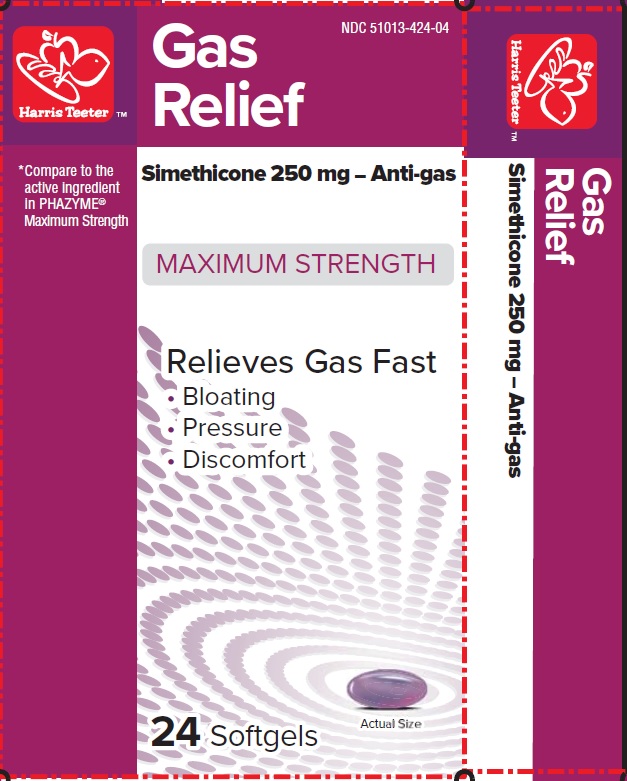 DRUG LABEL: Maximum Strength Gas Relief
NDC: 51013-424 | Form: CAPSULE, LIQUID FILLED
Manufacturer: PuraCap Pharmaceutical LLC
Category: otc | Type: HUMAN OTC DRUG LABEL
Date: 20171122

ACTIVE INGREDIENTS: DIMETHICONE 250 mg/1 1
INACTIVE INGREDIENTS: D&C RED NO. 33; FD&C BLUE NO. 1; GELATIN; GLYCERIN; WATER

MAXIMUM STRENGTH Gas Relief

Active ingredient (in each softgel)

Simethicone 250 mg

Purpose

Anti-gas

Use

relieves bloating, pressure or fullness commonly referred to as gas

Warnings

Stop use and ask a doctor if condition persists

Keep out of reach of children.

Directions

- swallow one or two softgels after a meal
- do not exceed two softgels per 24 hours except under the advice and supervision of a physician

Other information

- store at room temperature 59°-86°F (15°-30°C)

Inactive ingredients

D&C red #33, FD&C blue #1, gelatin, glycerin, purified water, and white edible ink

Questions or comments?

Call toll free: 1-800-719-9260

PRINCIPAL DISPLAY PANEL

MB MAXIMUM STRENGTH Gas Relief

SIMETHICONE 250 mg 24 SOFTGELS

NDC 51013-424-04

Compare to PHAZYME® Maximum Strength active ingredient*